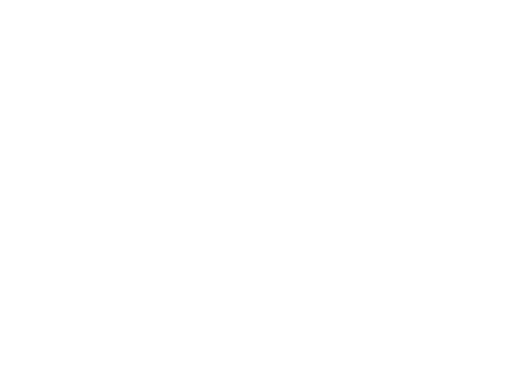 DRUG LABEL: Dorzolamide and Timolol
NDC: 55545-1007 | Form: SOLUTION
Manufacturer: FDC Limited
Category: prescription | Type: HUMAN PRESCRIPTION DRUG LABEL
Date: 20191115

ACTIVE INGREDIENTS: DORZOLAMIDE HYDROCHLORIDE 20 mg/1 mL; TIMOLOL MALEATE 5 mg/1 mL
INACTIVE INGREDIENTS: MANNITOL; SODIUM CITRATE; BENZALKONIUM CHLORIDE; SODIUM HYDROXIDE; WATER; HYDROXYETHYL CELLULOSE (2000 MPA.S AT 1%); HYDROXYETHYL CELLULOSE (4000 MPA.S AT 1%)

Dorzolamide hydrochloride and timolol maleate ophthalmic solution